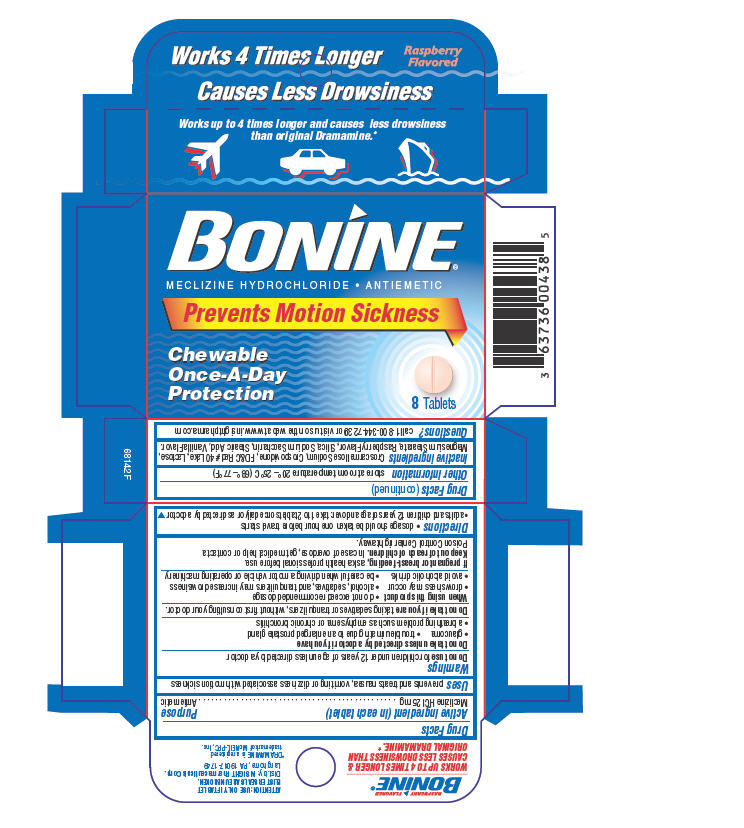 DRUG LABEL: Bonine
NDC: 63736-124 | Form: TABLET, CHEWABLE
Manufacturer: Insight Pharmaceuticals
Category: otc | Type: HUMAN OTC DRUG LABEL
Date: 20100111

ACTIVE INGREDIENTS: meclizine hydrochloride 25 mg/1 1
INACTIVE INGREDIENTS: crospovidone; FD&C Red No. 40; Aluminum Oxide; Lactose; Magnesium Stearate; Silicon Dioxide; Saccharin Sodium; stearic acid; Croscarmellose Sodium

BONINE®
MECLIZINE HYDROCHLORIDE • ANTIEMETIC

Drug Facts

Active ingredient (in each tablet)

Meclizine HCl 25 mg

Purpose

Antiemetic

Uses

prevents and treats nausea, vomiting or dizziness associated with motion sickness

Warnings

Do not use for children under 12 years of age unless directed by a doctor

ASK DOCTOR

Do not take unless directed by a doctor if you have

- glaucoma
- trouble urinating due to an enlarged prostate gland
- a breathing problem such as emphysema or chronic bronchitis

Do not take if you are taking sedatives or tranquilizers, without first consulting your doctor.

When using this product

- do not exceed recommended dosage
- drowsiness may occur
- alcohol, sedatives, and tranquilizers may increase drowsiness
- avoid alcoholic drinks
- be careful when driving a motor vehicle or operating machinery

PREGNANCY OR BREAST FEEDING

If pregnant or breast-feeding, ask a health professional before use.

Keep out of reach of children. In case of overdose, get medical help or contact a Poison Control Center right away.

Directions

- dosage should be taken one hour before travel starts
- adults and children 12 years of age and over: take 1 to 2 tablets once daily or as directed by a doctor

Other information

store at room temperature 20°– 25°C (68°–77°F)

Inactive ingredients

Croscarmellose Sodium, Crospovidone, FD&C Red #40 Lake, Lactose, Magnesium Stearate, Raspberry Flavor, Silica, Sodium Saccharin, Stearic Acid, Vanilla Flavor.

Questions?

call 1-800-344-7239 or visit us on the web at www.insightpharma.com

Dist. by: INSIGHT Pharmaceuticals Corp.
Langhorne, PA 19047-1749

PRINCIPAL DISPLAY PANEL - 8 Tablet Carton

BONINE®
MECLIZINE HYDROCHLORIDE • ANTIEMETIC

Prevents Motion Sickness

Chewable
Once-A-Day
Protection

8 Tablets